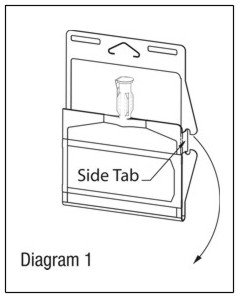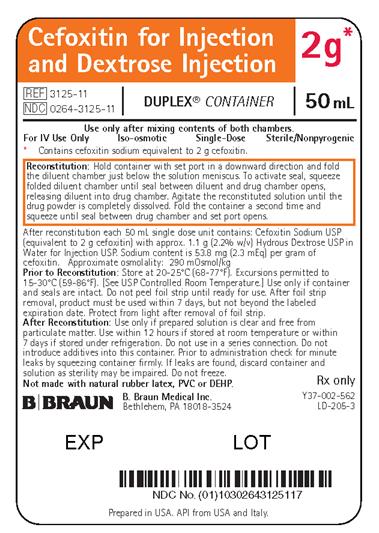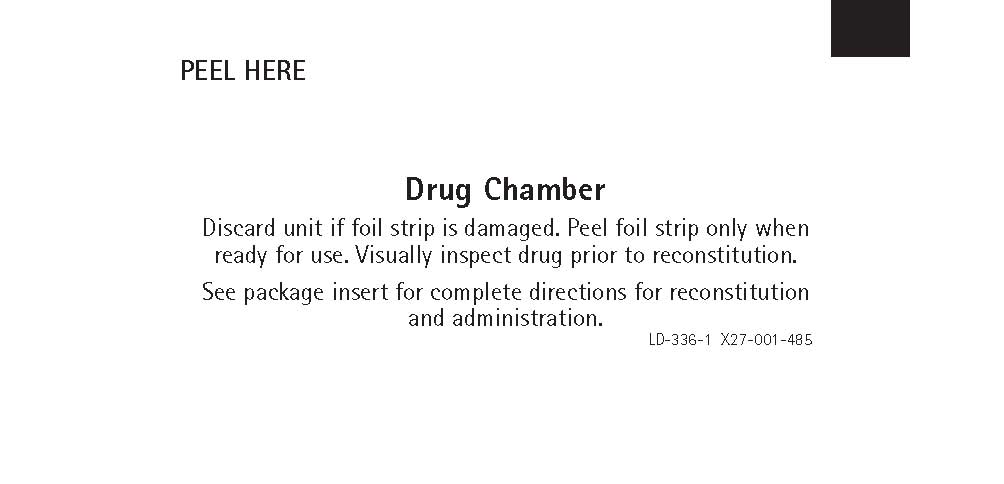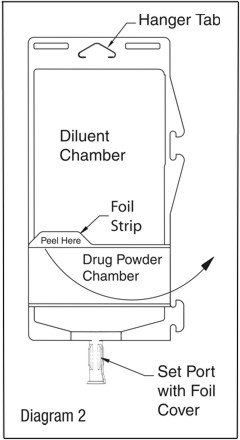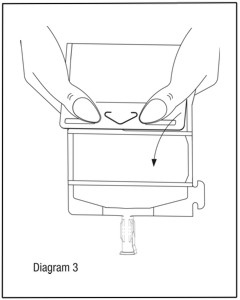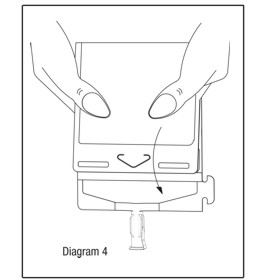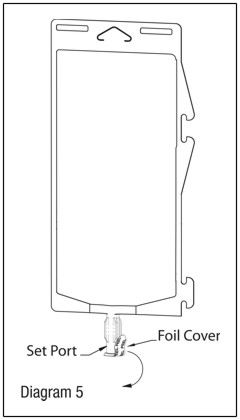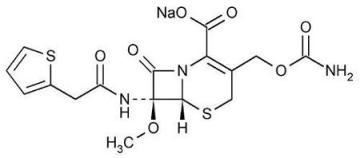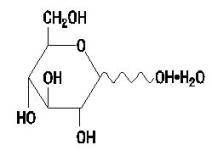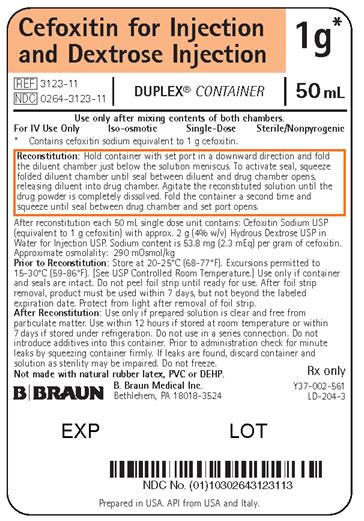 DRUG LABEL: Cefoxitin and Dextrose
NDC: 0264-3123 | Form: INJECTION, SOLUTION
Manufacturer: B. Braun Medical Inc.
Category: prescription | Type: HUMAN PRESCRIPTION DRUG LABEL
Date: 20190729

ACTIVE INGREDIENTS: CEFOXITIN SODIUM 1 g/50 mL
INACTIVE INGREDIENTS: DEXTROSE 2 g/50 mL; WATER

HIGHLIGHTS OF PRESCRIBING INFORMATION

These highlights do not include all the information needed to use CEFOXITIN for injection and DEXTROSE injection safely and effectively. See full prescribing information for CEFOXITIN for injection and DEXTROSE injection.
CEFOXITIN for injection and DEXTROSE injection,
for intravenous use
Initial U.S. Approval: 1978

1 INDICATIONS AND USAGE

Cefoxitin for Injection and Dextrose Injection is a cephalosporin antibacterial indicated for the treatment of the following infections caused by susceptible isolates of the designated bacteria (1):

- Lower respiratory tract infections (1.1);
- Urinary tract infections (1.2);
- Intra-abdominal infections (1.3);
- Gynecological infections (1.4);
- Septicemia (1.5);
- Bone and joint infections (1.6);
- Skin and skin structure infections (1.7);
- Prophylaxis (1.8).

To reduce the development of drug-resistant bacteria and maintain the effectiveness of Cefoxitin for Injection and Dextrose Injection and other antibacterial drugs, Cefoxitin for Injection and Dextrose Injection should be used only to treat or prevent infections that are proven or strongly suspected to be caused by bacteria (1.9).

2 DOSAGE AND ADMINISTRATION

- For intravenous use only. (2)
- Use this formulation of cefoxitin only in patients who require the entire 1 or 2 gram dose and not any fraction thereof. (2.3)
- See full prescribing information for dose adjustment in patients with impaired renal function. (2.3)
- Recommended dosing schedule in patients with normal renal function. (2.1)

3 DOSAGE FORMS AND STRENGTHS

Single-dose DUPLEX® Container consisting of:

- 1 g cefoxitin for injection and 50 mL 5% dextrose injection (3)
- 2 g cefoxitin for injection and 50 mL 5% dextrose injection (3)

4 CONTRAINDICATIONS

- Hypersensitivity to cefoxitin or other beta-lactam antibacterial drugs. (4.1)
- Hypersensitivity to corn products. (4.2)

5 WARNINGS AND PRECAUTIONS

- Hypersensitivity reactions including anaphylaxis and serious skin reactions. If an allergic reaction occurs, discontinue the drug. (5.1)
- Use in patients with renal impairment: Dosage adjustment required for patients with impaired renal function. (2.3)
- Clostridium difficile-associated diarrhea: May range from mild diarrhea to fatal colitis. Evaluate if diarrhea occurs. (5.2)

6 ADVERSE REACTIONS

- Most common adverse reactions: Local reactions. (6)

To report SUSPECTED ADVERSE REACTIONS, contact B. Braun Medical Inc. at 1-800-854-6851 or FDA at 1-800-FDA-1088 or www.fda.gov/medwatch.

7 DRUG INTERACTIONS

- Aminoglycosides: Increased potential of nephrotoxicity. (7.1)

8 USE IN SPECIFIC POPULATIONS

- Pediatric use: Safety and efficacy of this formulation not established (8.4)

FULL PRESCRIBING INFORMATION

1 INDICATIONS AND USAGE

1.1 Lower Respiratory Tract Infections

Cefoxitin for Injection and Dextrose Injection is indicated for the treatment of lower respiratory tract infections, including pneumonia and lung abscess, caused by Streptococcus pneumoniae, other streptococci (excluding enterococci, e.g., Enterococcus faecalis [formerly Streptococcus faecalis]), Staphylococcus aureus (including penicillinase-producing strains), Escherichia coli, Klebsiella species, Haemophilus influenzae, and Bacteroides species.

1.2 Urinary Tract Infections

Cefoxitin for Injection and Dextrose Injection is indicated for the treatment of urinary tract infections caused by Escherichia coli, Klebsiella species, Proteus mirabilis, Morganella morganii, Proteus vulgaris and Providencia species (including P. rettgeri).

1.3 Intra-abdominal Infections

Cefoxitin for Injection and Dextrose Injection is indicated for the treatment of intra-abdominal infections, including peritonitis and intra-abdominal abscess, caused by Escherichia coli, Klebsiella species, Bacteroides species including Bacteroides fragilis, and Clostridium species.

1.4 Gynecological Infections

Cefoxitin for Injection and Dextrose Injection is indicated for the treatment of gynecological infections, including endometritis, pelvic cellulitis, and pelvic inflammatory disease caused by Escherichia coli, Neisseria gonorrhoeae (including penicillinase-producing strains), Bacteroides species including B. fragilis, Clostridium species, Peptococcus niger, Peptostreptococcus species, and Streptococcus agalactiae.

Cefoxitin has no activity against Chlamydia trachomatis. Therefore, when cefoxitin is used in the treatment of patients with pelvic inflammatory disease and C. trachomatis is one of the suspected pathogens, appropriate anti-chlamydial coverage should be added.

1.5 Septicemia

Cefoxitin for Injection and Dextrose Injection is indicated for the treatment of Septicemia caused by Streptococcus pneumoniae, Staphylococcus aureus (including penicillinase-producing strains), Escherichia coli, Klebsiella species, and Bacteroides species including B. fragilis.

1.6 Bone and Joint Infections

Cefoxitin for Injection and Dextrose Injection is indicated for the treatment of bone and joint infections caused by Staphylococcus aureus (including penicillinase-producing strains).

1.7 Skin and Skin Structure Infections

Cefoxitin for Injection and Dextrose Injection is indicated for the treatment of skin and skin structure infections caused by Staphylococcus aureus (including penicillinase-producing strains), Staphylococcus epidermidis, Streptococcus pyogenes and other streptococci (excluding enterococci, e.g., Enterococcus faecalis [formerly Streptococcus faecalis]), Escherichia coli, Proteus mirabilis, Klebsiella species, Bacteroides species including B. fragilis, Clostridium species, Peptococcus niger, and Peptostreptococcus species.

1.8 Prophylaxis

Cefoxitin for Injection and Dextrose Injection is indicated for the prophylaxis of infection in patients undergoing uncontaminated gastrointestinal surgery, vaginal hysterectomy, abdominal hysterectomy, or cesarean section.

If there are signs of infection, specimens for culture should be obtained for identification of the causative organism so that appropriate treatment may be instituted.

1.9 Usage

To reduce the development of drug-resistant bacteria and maintain the effectiveness of Cefoxitin for Injection and Dextrose Injection and other antibacterial drugs, Cefoxitin for Injection and Dextrose Injection should be used only to treat or prevent infections that are proven or strongly suspected to be caused by susceptible bacteria. When culture and susceptibility information are available, they should be considered in selecting or modifying antibacterial therapy. In the absence of such data, local epidemiology and susceptibility patterns may contribute to the empiric selection of therapy.

2 DOSAGE AND ADMINISTRATION

2.1 Dosage in Adults for Treatment

The usual adult dosage range is 1 gram to 2 grams every six to eight hours. Dosage should be determined by susceptibility of the causative organisms, severity of infection, and the condition of the patient (see Table 1 for dosage guidelines). Administer Cefoxitin for Injection and Dextrose Injection intravenously over approximately 30 minutes.

If C. trachomatis is a suspected pathogen, appropriate anti-chlamydial coverage should be added, because cefoxitin sodium has no activity against this organism [see Indications and Usage (1.4)].

Antibacterial therapy for group A beta-hemolytic streptococcal infections should be maintained for at least 10 days to guard against the risk of rheumatic fever or glomerulonephritis.

In staphylococcal and other infections involving a collection of pus, surgical drainage should be carried out where indicated.

Use this formulation of cefoxitin only in patients who require the entire 1 or 2 gram dose and not any fraction thereof.

Table 1: Guidelines for Dosage of Cefoxitin for Injection
Type of Infection | Daily Dosage | Frequency and Route
Uncomplicated forms [Including patients in whom bacteremia is absent or unlikely.] of infections such as pneumonia, urinary tract infection, cutaneous infection | 3-4 grams | 1 gram every 6-8 hours IV
Moderately severe or severe infections | 6-8 grams | 1 gram every 4 hours or 2 grams every 6-8 hours IV
Infections commonly needing antibacterial drugs in higher dosage (e.g., gas gangrene) | 12 grams | 2 grams every 4 hours or 3 grams every 6 hours IV

2.2 Dosage in Adults for Prophylaxis

Effective prophylactic use depends on the time of administration. Cefoxitin for Injection and Dextrose Injection usually should be given one-half to one hour before the operation, which is sufficient time to achieve effective levels in the wound during the procedure. Prophylactic administration should usually be stopped within 24 hours since continuing administration of any antibacterial increases the possibility of adverse reactions but, in the majority of surgical procedures, does not reduce the incidence of subsequent infection.

For prophylactic use in uncontaminated gastrointestinal surgery, vaginal hysterectomy, or abdominal hysterectomy, the following doses are recommended:

• 2 grams administered intravenously just prior to surgery (approximately one-half to one hour
before the initial incision) followed by
• 2 grams every 6 hours after the first dose for no more than 24 hours.

For patients undergoing cesarean section, either a single 2 gram dose administered intravenously as soon as the umbilical cord is clamped OR a 3-dose regimen consisting of 2 grams given intravenously as soon as the umbilical cord is clamped followed by 2 grams 4 and 8 hours after the initial dose is recommended [see Clinical Studies (14.1)].

2.3 Dosage in Patients with Renal Impairment

In adults with renal impairment, an initial loading dose of 1 gram to 2 grams may be given. After a loading dose, the recommendations for maintenance dosage (Table 2) may be used as a guide.

When only the serum creatinine level is available, the following formula (based on sex, weight, and age of the patient) may be used to convert this value into creatinine clearance. The serum creatinine should represent a steady state of renal function.

Males: Weight (kg) x (140 - age)

72 x serum creatinine (mg/100 mL)

Females: 0.85 x above value

In patients undergoing hemodialysis, the loading dose of 1 to 2 grams should be given after each hemodialysis, and the maintenance dose should be given as indicated in Table 2.

Table 2: Maintenance Dosage of Cefoxitin for Injection in Adults with Renal Impairment
Renal Function | Creatinine Clearance (mL/min) | Dose (grams) | Frequency
Mild impairment Moderate impairment Severe impairment Essentially no function | 50-30 29-10 9-5 <5 | 1-2 1-2 0.5-1 0.5-1 | every 8-12 hours every 12-24 hours every 12-24 hours every 24-48 hours

2.4 Preparation and Administration of Cefoxitin for Injection and Dextrose Injection in DUPLEX® Container

Important Administration Instructions

• This reconstituted solution is for intravenous use only.

• Administer Cefoxitin for Injection and Dextrose Injection intravenously over approximately 30 minutes.

• Do not use in series connections. Such use would result in air embolism due to residual air being drawn from the primary container before administration of the fluid from the secondary container is complete. If administration is controlled by a pumping device, care must be taken to discontinue pumping action before the container runs dry or air embolism may result.

• Do not introduce additives into the DUPLEX® Container.

• Cefoxitin for Injection and Dextrose Injection may be administered through the tubing system by which the patient may be receiving other intravenous solutions. However, during infusion of the solution containing Cefoxitin for Injection and Dextrose Injection, it is advisable to temporarily discontinue administration of any other solutions at the same site.

• Cefoxitin for Injection and Dextrose Injection, like most beta-lactam antibiotics, should not be added to aminoglycoside solutions (e.g., gentamicin sulfate, tobramycin sulfate, amikacin sulfate) because of potential interaction. However, Cefoxitin for Injection and Dextrose Injection and aminoglycosides may be administered separately to the same patient.

Parenteral drug products should be inspected visually for particulate matter and discoloration
prior to administration, whenever solution and container permit.

Use only if solution is clear and free from particulate matter and container and seals are intact. As with other cephalosporins, reconstituted Cefoxitin for Injection and Dextrose Injection tends to darken depending on storage conditions, within the stated recommendations. However, product potency is not adversely affected.

DUPLEX® Container Storage

• To avoid inadvertent activation, DUPLEX® Container should remain in the folded position until activation is intended.

Patient Labeling and Drug Powder/Diluent Inspection

• Apply patient-specific label on foil side of container. Use care to avoid activation. Do not cover any portion of foil strip with patient label.

• Unlatch side tab and unfold DUPLEX® Container (see Diagram 1).

• Visually inspect diluent chamber for particulate matter.

• Use only if container and seals are intact.

• To inspect the drug powder for foreign matter or discoloration, peel foil strip from drug chamber (see Diagram 2).

• Protect from light after removal of foil strip.

• Note: If foil strip is removed, the container should be re-folded and the side tab latched until ready to activate. The product must then be used within 7 days, but not beyond the labeled expiration date.

Reconstitution (Activation)

• Do not use directly after storage by refrigeration, allow the product to equilibrate to room temperature before patient use.

• Unfold the DUPLEX® Container and point the set port in a downward direction. Starting at the hanger tab end, fold the DUPLEX® Container just below the diluent meniscus trapping all air above the fold. To activate, squeeze the folded diluent chamber until the seal between the diluent and powder opens, releasing diluent into the drug powder chamber (see Diagram 3).

• Agitate the liquid-powder mixture until the drug powder is completely dissolved.

Note: Following reconstitution (activation), product must be used within 12 hours if stored at room temperature or within 7 days if stored under refrigeration.

Administration

• Visually inspect the reconstituted solution for particulate matter.

• Point the set port in a downwards direction. Starting at the hanger tab end, fold the DUPLEX® Container just below the solution meniscus trapping all air above the fold. Squeeze the folded DUPLEX® Container until the seal between reconstituted drug solution and set port opens, releasing liquid to set port (see Diagram 4).

• Prior to attaching the IV set, check for minute leaks by squeezing container firmly. If leaks are found, discard container and solution as sterility may be compromised.

• Using aseptic technique, peel foil cover from the set port and attach sterile administration set (see Diagram 5).

• Refer to Directions for Use accompanying the administration set.

• Discard unused portions.

3 DOSAGE FORMS AND STRENGTHS

Single-dose DUPLEX® (Dual-chamber), Container:

• 1 g cefoxitin for injection and 50 mL of 5% dextrose injection

• 2 g cefoxitin for injection and 50 mL of 5% dextrose injection

4 CONTRAINDICATIONS

4.1 Hypersensitivity to Cefoxitin or other Beta-lactam Antibacterial Drugs

Cefoxitin for Injection and Dextrose Injection is contraindicated in patients who have shown hypersensitivity to cefoxitin or to other β-lactam antibacterial drugs (e.g., penicillins and cephalosporins).

4.2 Hypersensitivity to Corn Products

Solutions containing dextrose may be contraindicated in patients with hypersensitivity to corn products.

5 WARNINGS AND PRECAUTIONS

5.1 Hypersensitivity Reactions to Cefoxitin or other Beta-lactam Antibacterial Drugs

Serious and occasionally fatal hypersensitivity reactions (e.g., anaphylaxis) have been reported in patients on β-lactam antibacterials, including cefoxitin [see Adverse Reactions (6.1)]. These reactions are more likely to occur in individuals with a history of β-lactam hypersensitivity and/or a history of sensitivity to multiple allergens. There have been reports of individuals with a history of penicillin hypersensitivity who have experienced severe reactions when treated with cephalosporins. Cefoxitin for Injection and Dextrose Injection is contraindicated in patients with a known hypersensitivity to Cefoxitin for Injection and Dextrose Injection or other β-lactam antibacterial drugs [see Contraindications (4)]. Before initiating therapy with Cefoxitin for Injection and Dextrose Injection, inquire about previous hypersensitivity reactions to penicillins, cephalosporins, or other allergens. If an allergic reaction occurs, discontinue Cefoxitin for Injection and Dextrose Injection and institute appropriate therapy.

5.2 Clostridium difficile-associated Diarrhea

Clostridium difficile associated diarrhea (CDAD) has been reported with use of nearly all antibacterial agents, including Cefoxitin for Injection and Dextrose Injection, and may range in severity from mild diarrhea to fatal colitis. Treatment with antibacterial agents alters the normal flora of the colon leading to overgrowth of C. difficile.

C. difficile produces toxins A and B which contribute to the development of CDAD. Hypertoxin producing strains of C. difficile cause increased morbidity and mortality, as these infections can be refractory to antimicrobial therapy and may require colectomy. CDAD must be considered in all patients who present with diarrhea following antibiotic use. Careful medical history is necessary since CDAD has been reported to occur over two months after the administration of antibacterial agents.

If CDAD is suspected or confirmed, ongoing antibiotic use not directed against C. difficile may need to be discontinued. Appropriate fluid and electrolyte management, protein supplementation, antibiotic treatment of C. difficile, and surgical evaluation should be instituted as clinically indicated.

5.3 Risk of Development of Drug-resistant Bacteria

Prescribing Cefoxitin for Injection and Dextrose Injection in the absence of a proven or strongly suspected bacterial infection or a prophylactic indication is unlikely to provide benefit to the patient and increases the risk of the development of drug-resistant bacteria.

Prolonged use of Cefoxitin for Injection and Dextrose Injection may result in overgrowth of non-susceptible microorganisms. Repeated evaluation of the patient's condition is essential. Should superinfection occur during therapy, appropriate measures should be taken.

5.4 Drug/Laboratory Test Interactions

As with cephalothin, high concentrations of cefoxitin (>100 mcg/mL) may interfere with measurement of serum and urine creatinine levels by Jaffé reaction, and produce false increases of modest degree in the levels of creatinine reported. Serum samples from patients treated with cefoxitin should not be analyzed for creatinine if withdrawn within 2 hours of drug administration.

High concentrations of cefoxitin in the urine may interfere with measurement of urinary 17-hydroxy-corticosteroids by the Porter-Silber reaction, and produce false increases of modest degree in the levels reported.

A false-positive reaction for glucose in the urine may occur. This has been observed with CLINITEST® reagent tablets.

5.5 Patients with a History of Gastrointestinal Disease

Cefoxitin for Injection and Dextrose Injection is not recommended in individuals with a history of gastrointestinal disease, particularly colitis.

5.6 Patients with Overt or Known Subclinical Diabetes Mellitus or Carbohydrate Intolerance

As with other dextrose-containing solutions, Cefoxitin for Injection and Dextrose Injection should be monitored if Cefoxitin for Injection and Dextrose Injection is prescribed in patients with overt or known subclinical diabetes mellitus or carbohydrate intolerance for any reason.

6 ADVERSE REACTIONS

The following clinically significant adverse reactions are discussed in greater detail in other sections of labeling:

• Hypersensitivity Reactions to Cefoxitin or other Beta-lactam Antibacterial Drugs [see Warnings and Precautions (5.1)]

• Use in Patients with Renal Impairment [see Dosage and Administration (2.3), Use in Specific Populations (8.6)]

• Clostridium difficile-associated Diarrhea [see Warnings and Precautions (5.2)]

• Risk of Development of Drug-resistant Bacteria [see Warnings and Precautions (5.3)]

• Drug/Laboratory Test Interactions [see Warnings and Precautions (5.4)]

• Patients with a History of Gastrointestinal Disease [see Warnings and Precautions (5.5)]

• Patients with Overt or Known Subclinical Diabetes Mellitus or Carbohydrate Intolerance [see Warnings and Precautions (5.6)]

The most common adverse reactions have been local reactions following intravenous injection.

Local Reactions

Thrombophlebitis has occurred with intravenous administration.

Skin and Subcutaneous Tissue Disorders

Rash (including exfoliative dermatitis and toxic epidermal necrolysis), urticaria, flushing, pruritus, eosinophilia, fever, dyspnea, and other allergic reactions including anaphylaxis, interstitial nephritis and angioedema have been noted.

Cardiovascular Disorders

Hypotension.

Gastrointestinal Disorders

Diarrhea, including documented pseudomembranous colitis which can appear during or after antibiotic treatment. Nausea and vomiting have been reported.

Nervous System Disorders

Possible exacerbation of myasthenia gravis.

Blood and Lymphatic System Disorders

Eosinophilia, leukopenia including granulocytopenia, neutropenia, anemia including hemolytic anemia, thrombocytopenia, and bone marrow depression. A positive direct Coombs test may develop in some individuals, especially those with azotemia.

Hepatobiliary Disorders

Reversible elevation in SGOT, SGPT, serum LDH, and serum alkaline phosphatase; and jaundice have been reported.

Renal and Urinary Disorders

Elevations in serum creatinine and/or blood urea nitrogen levels have been observed. Acute renal failure has been reported.

6.1 Cephalosporin-class Adverse Reactions

In addition to the adverse reactions listed above which have been observed in patients treated with cefoxitin, the following adverse reactions and altered laboratory test results have been reported for cephalosporin class antibacterials: pruritus, Stevens-Johnson syndrome, erythema multiforme, toxic epidermal necrolysis, vomiting, abdominal pain, colitis, superinfection, vaginitis including vaginal candidiasis, renal dysfunction, toxic nephropathy, hepatic dysfunction including cholestasis, aplastic anemia, hemorrhage, elevated bilirubin, pancytopenia, and neutropenia.

Several cephalosporins, including Cefoxitin for Injection and Dextrose Injection, have been implicated in triggering seizures, particularly in patients with renal impairment, when the dosage was not reduced [see Dosage and Administration (2.3) and Overdosage (10)]. If seizures associated with drug therapy occur, the drug should be discontinued. Anticonvulsant therapy can be given if clinically indicated.

7 DRUG INTERACTIONS

7.1 Aminoglycosides

Increased nephrotoxicity has been reported following concomitant administration of cephalosporins and aminoglycoside antibacterials.

8 USE IN SPECIFIC POPULATIONS

8.1 Pregnancy

Risk Summary

Available data from published prospective cohort studies, case series, and case reports over several decades with cephalosporin use, including cefoxitin, in pregnant women have not established drug-associated risks of major birth defects, miscarriage, or adverse maternal or fetal outcomes (see Data). In animal reproduction studies, no adverse developmental effects were observed in pregnant rats and mice administered parenteral doses of cefoxitin at approximately 1 to 7.5 times the maximum recommended human dose (see Data).

The estimated background risk of major birth defects and miscarriage for the indicated population is unknown. All pregnancies have a background risk of birth defect, loss, or other adverse outcomes. In the U.S. general population, the estimated background risk of major birth defects and miscarriage in clinically recognized pregnancies is 2-4% and 15-20%, respectively. Cefoxitin is found in umbilical cord blood and amniotic fluid after maternal administration.

Clinical Considerations

Disease-Associated Maternal and/or Embryo/Fetal Risk

Maternal gonorrhea may be associated with preterm birth, low neonatal birth weight, chorioamnionitis, intrauterine growth restriction, small for gestational age and premature rupture of membranes. Perinatal transmission of gonorrhea to the offspring can result in infant blindness, joint infections and bloodstream infections.

Data

Human Data

While available studies cannot definitively establish the absence of risk, published data from prospective cohort studies, case series, and case reports over several decades have not identified an association with cephalosporin use, including cefoxitin, during pregnancy, and major birth defects, miscarriage, or other adverse maternal or fetal outcomes.

Available studies have methodologic limitations, including small sample size, retrospective data collection, and inconsistent comparator groups.

Animal Data

Reproduction studies performed in pregnant rats and mice at parenteral doses of approximately one to seven and one-half times the maximum recommended human dose did not reveal teratogenic or fetal toxic effects, although a slight decrease in fetal weight was observed.

In the rabbit, cefoxitin was associated with a high incidence of abortion and maternal death. This was not considered to be a teratogenic effect but an expected consequence of the rabbit’s unusual sensitivity to antibiotic-induced changes in the population of the microflora of the intestine.

8.2 Lactation

Risk Summary

Limited data from published literature report the presence of cefoxitin in human milk. For an infant fed exclusively with human milk, the estimated infant daily dose through breastfeeding is less than 0.1% of maternal daily IV dose (see Data). Minimal data are available on the effects of the drug on the breastfed infant; none of these reports suggest serious safety concerns. No data are available on the effects of the drug on milk production. The developmental and health benefits of breastfeeding should be considered along with the mother’s clinical need for cefoxitin and any potential adverse effects on the breastfed infant from cefoxitin or from the underlying maternal condition.

Data

In a published clinical lactation study, the concentration of cefoxitin ranged from 11.6 ± 0.8 to 0.49 ± 0.01 mcg/mL and 1.71 ± 0.08 to 0.57 ± 0.02 mcg/mL in human plasma and breast milk, respectively, at 1, 1.5, 2 or 2.5 hours following IV administration of 1 g cefoxitin twice daily.

8.4 Pediatric Use

Safety and efficacy of this formulation are not established. This formulation of cefoxitin is indicated for use only in patients who require the entire 1 or 2 gram dose.

8.5 Geriatric Use

Of the 1,775 subjects who received cefoxitin in clinical studies, 424 (24%) were 65 and over, while 124 (7%) were 75 and over. No overall differences in safety or effectiveness were observed between these subjects and younger subjects, and other reported clinical experience has not identified differences in responses between the elderly and younger patients, but greater sensitivity of some older individuals cannot be ruled out [see Clinical Pharmacology (12.3)].

This drug is known to be substantially excreted by the kidney, and the risk of toxic reactions to this drug may be greater in patients with impaired renal function. Because elderly patients are more likely to have decreased renal function, care should be taken in dose selection, and it may be useful to monitor renal function [see Dosage and Administration (2.3), and Clinical Pharmacology (12.3)].

8.6 Renal Impairment

In patients with a reduced creatinine clearance the dose of Cefoxitin Injection and Dextrose Injection should be adjusted to compensate for the slower rate of renal elimination. Because high and prolonged cefoxitin concentrations can occur from usual dosages in patients with renal impairment or other conditions that may compromise renal function, the maintenance dosage should be reduced when Cefoxitin Injection and Dextrose Injection is administered to such patients. Continued dosage should be determined by the degree of renal impairment, severity of infection, and susceptibility of the causative organisms [see Dosage and Administration (2.3)].

10 OVERDOSAGE

Information on overdosage with Cefoxitin for Injection and Dextrose Injection in humans is not available. If overdosage should occur, it should be treated symptomatically.

11 DESCRIPTION

Cefoxitin for Injection and Dextrose Injection is a sterile, nonpyrogenic, single-dose packaged combination of cefoxitin sodium USP and Dextrose Injection (diluent) in the DUPLEX® sterile container. The DUPLEX® Container is a flexible dual chamber container.

The drug chamber is filled with cefoxitin sodium USP, a semi-synthetic, broad-spectrum cephalosporin antibacterial sealed under nitrogen for intravenous administration. Cefoxitin sodium USP is derived from cephamycin C, which is produced by Streptomyces lactamdurans. Its chemical name is sodium (6R,7S)-3-(hydroxymethyl)-7-methoxy-8-oxo-7-[2-(2-thienyl)acetamido]-5-thia-1-azabicyclo[4.2.0]oct-2-ene-2-carboxylate carbamate (ester).

The empirical formula is C16H16N3NaO7S2, and the molecular weight is 449.44. The structural formula is:

Cefoxitin sodium contains approximately 53.8 mg (2.3 mEq) of sodium per gram of cefoxitin activity.

The diluent chamber contains Dextrose Injection. The concentration of Dextrose Hydrous USP in Water for Injection USP has been adjusted to render the reconstituted drug product iso-osmotic. Dextrose Hydrous USP has been added to adjust the osmolality to approximately 290 mOsmol/kg (approximately 2 g (4% w/v) and 1.1 g (2.2% w/v) to the 1 g and 2 g doses, respectively). Dextrose Injection is sterile, nonpyrogenic, and contains no bacteriostatic and antimicrobial agents.

Dextrose Hydrous USP has the following structural (molecular) formula:

The molecular weight of Dextrose Hydrous USP is 198.17.

After removing the peelable foil strip, activating the seals, and thoroughly mixing, the reconstituted drug product is intended for single intravenous use. When reconstituted according to instructions in the product labeling, the approximate osmolality of the reconstituted solution of Cefoxitin for Injection and Dextrose Injection is approximately 290 mOsmol/kg. After reconstitution, each 50 mL contains 1 gram of cefoxitin (equivalent to 1.05 gram of cefoxitin sodium) or 2 grams of cefoxitin (equivalent to 2.10 grams of cefoxitin sodium), with a pH of approximately 6.5. Solutions of Cefoxitin for Injection and Dextrose Injection range from colorless to light amber.

The DUPLEX® dual chamber container is made from a specially formulated material. The product (diluent and drug) contact layer is a mixture of thermoplastic rubber and a polypropylene ethylene copolymer that contains no plasticizers. The safety of the container system is supported by USP biological evaluation procedures.

12 CLINICAL PHARMACOLOGY

12.1 Mechanism of Action

Cefoxitin is an antibacterial drug [see Microbiology (12.4)].

12.2 Pharmacodynamics

The pharmacodynamic properties of cefoxitin are unknown.

12.3 Pharmacokinetics

Absorption

Following an intravenous dose of 1 gram, serum concentrations were 110 mcg/mL at 5 minutes, declining to less than 1 mcg/mL at 4 hours.

Distribution

Cefoxitin passes into pleural and joint fluids and is detectable in antibacterial concentrations in bile.

Elimination

Metabolism

The half-life after an intravenous dose is 41 to 59 minutes.

Excretion

Approximately 85 percent of cefoxitin is excreted unchanged by the kidneys over a 6-hour period, resulting in high urinary concentrations. Probenecid slows tubular excretion and produces higher serum levels and increases the duration of measurable serum concentrations.

Specific Populations

Geriatric Patients

In a published study of geriatric patients ranging in age from 64 to 88 years with normal renal function for their age (creatinine clearance ranging from 31.5 to 174.0 mL/min), the half-life for cefoxitin ranged from 51 to 90 minutes, resulting in higher plasma concentrations than in younger adults. These changes were attributed to decreased renal function associated with the aging process.

12.4 Microbiology

Mechanism of Action

Cefoxitin is a bactericidal agent that acts by inhibition of bacterial cell wall synthesis. Cefoxitin has activity in the presence of some beta-lactamases, both penicillinases and cephalosporinases, of Gram-negative and Gram-positive bacteria.

Resistance

Resistance to Cefoxitin is primarily through hydrolysis by beta-lactamase, alteration of penicillin-binding proteins (PBPs), and decreased permeability.

Antimicrobial Activity

Cefoxitin has been shown to be active against most isolates of the following microorganisms, both in vitro and in clinical infections [see Indications and Usage (1)].

Gram-positive bacteria

Staphylococcus aureus
Staphylococcus epidermidis
Streptococcus agalactiae
Streptococcus pneumoniae
Streptococcus pyogenes

Gram-negative bacteria

Escherichia coli
Haemophilus influenzae
Klebsiella spp.
Morganella morganii
Neisseria gonorrhoeae
Proteus mirabilis
Proteus vulgaris
Providencia spp.

Anaerobic bacteria

Clostridium spp.
Peptococcus niger
Peptostreptococcus spp.
Bacteroides distasonis
Bacteroides fragilis
Bacteroides ovatus
Bacteroides thetaiotaomicron
Bacteroides spp.

The following in vitro data are available, but their clinical significance is unknown. At least 90 percent of the following bacteria exhibit an in vitro minimum inhibitory concentration (MIC) less than or equal to the susceptible breakpoint for cefoxitin against isolates of similar genus or organism group. However, the efficacy of cefoxitin in treating clinical infections caused by these bacteria has not been established in adequate and well-controlled clinical trials.

Gram-negative bacteria

Eikenella corrodens [non- β-lactamase producers]

Anaerobic bacteria

Clostridium perfringens
Prevotella bivia

Susceptibility Testing

For specific information regarding susceptibility test interpretive criteria, and associated test methods and quality control standards recognized by FDA for this drug, please see: http://www.fda.gov/STIC.

13 NONCLINICAL TOXICOLOGY

13.1 Carcinogenesis, Mutagenesis, Impairment of Fertility

Carcinogenesis

Long term studies in animals have not been performed with cefoxitin to evaluate carcinogenic potential.

Mutagenesis

Long term studies in animals have not been performed with cefoxitin to evaluate mutagenic potential.

Impairment of Fertility

Studies in rats treated intravenously with 400 mg/kg of cefoxitin (approximately three times the maximum recommended human dose) revealed no effects on fertility or mating ability.

14 CLINICAL STUDIES

14.1 Prophylaxis

A prospective, randomized, double-blind, placebo-controlled clinical trial was conducted to determine the efficacy of short-term prophylaxis with cefoxitin in patients undergoing cesarean section who were at high risk for subsequent endometritis because of ruptured membranes. Patients were randomized to receive either three doses of placebo (n=58), a single dose of cefoxitin (2 g) followed by two doses of placebo (n=64), or a three-dose regimen of cefoxitin (each dose consisting of 2 g) (n=60), given intravenously, usually beginning at the time of clamping of the umbilical cord, with the second and third doses given 4 and 8 hours post-operatively. Endometritis occurred in 16/58 (27.6%) patients given placebo, 5/63 (7.9%) patients given a single dose of cefoxitin, and 3/58 (5.2%) patients given three doses of cefoxitin. The differences between the two groups treated with cefoxitin and placebo with respect to endometritis were statistically significant (p<0.01) in favor of cefoxitin. The differences between the one-dose and three-dose regimens of cefoxitin were not statistically significant.

Two double-blind, randomized studies compared the efficacy of a single 2 gram intravenous dose of cefoxitin to a single 2 gram intravenous dose of cefotetan in the prevention of surgical site-related infection (major morbidity) and non-site-related infections (minor morbidity) in patients following cesarean section. In the first study, 82/98 (83.7%) patients treated with cefoxitin and 71/95 (74.7%) patients treated with cefotetan experienced no major or minor morbidity. The difference in the outcomes in this study (95% CI: -0.03, +0.21) was not statistically significant. In the second study, 65/75 (86.7%) patients treated with cefoxitin and 62/76 (81.6%) patients treated with cefotetan experienced no major or minor morbidity. The difference in the outcomes in this study (95% CI: -0.08, +0.18) was not statistically significant.

14.2 Intra-abdominal Infections

In clinical trials of patients with intra-abdominal infections due to Bacteroides fragilis group microorganisms, eradication rates at 1 to 2 weeks post-treatment for isolates were in the range of 70% to 80%. Eradication rates for individual species are listed below:

Bacteroides distasonis 7/10 (70%)

Bacteroides fragilis 26/33 (79%)

Bacteroides ovatus 10/13 (77%)

B. thetaiotaomicron 13/18 (72%)

16 HOW SUPPLIED/STORAGE AND HANDLING

How Supplied

Cefoxitin for Injection and Dextrose Injection in the DUPLEX® Container is a flexible dual chamber single-dose container supplied in two concentrations. After reconstitution, the delivered doses are equivalent to 1 g and 2 g cefoxitin. The diluent chamber contains approximately 50 mL of Dextrose Injection. Dextrose Injection has been adjusted to 4% w/v and 2.2% w/v for the 1 g and 2 g doses, respectively, such that the reconstituted solution is iso-osmotic.

Cefoxitin for Injection and Dextrose Injection is supplied sterile and nonpyrogenic in the DUPLEX® Container packaged 24 units per case.

NDC | REF | Dose | Volume
0264-3123-11 | 3123-11 | 1 g | 50 mL
0264-3125-11 | 3125-11 | 2 g | 50 mL

Not made with natural rubber latex, PVC or Di(2-ethylhexyl)phthalate (DEHP).

Storage

Store the unactivated unit at 20-25°C (68-77°F). Excursions permitted to 15-30°C (59-86°F). [See USP Controlled Room Temperature.] Do not freeze.

As with other cephalosporins, reconstituted Cefoxitin for Injection and Dextrose Injection tends to darken depending on storage conditions, within the stated recommendations. However, product potency is not adversely affected.

Use only if prepared solution is clear and free from particulate matter.

17 PATIENT COUNSELING INFORMATION

Allergic Reactions

Inform patients that Cefoxitin for Injection and Dextrose Injection is a cephalosporin that can cause allergic reactions in some individuals [see Warnings and Precautions (5.1)].

Clostridium difficile-Associated Diarrhea

Inform patients that diarrhea is a common problem caused by antibacterials, including Cefoxitin for Injection and Dextrose Injection, and it usually ends when the antibacterial is discontinued.

Sometimes after starting treatment with antibacterials, patients can develop watery and bloody stools (with or without stomach cramps and fever) even as late as 2 or more months after having taken their last dose of the antibacterial. If this occurs, advise patients to contact their physician as soon as possible.

Drug Resistance

Patients should be counseled that antibacterial drugs including Cefoxitin for Injection and Dextrose Injection should only be used to treat bacterial infections. They do not treat viral infections (e.g., the common cold). When Cefoxitin for Injection and Dextrose Injection is prescribed to treat a bacterial infection, patients should be told that although it is common to feel better early in the course of therapy, the medication should be taken exactly as directed. Skipping doses or not completing the full course of therapy may: (1) decrease the effectiveness of the immediate treatment, and (2) increase the likelihood that bacteria will develop resistance and will not be treatable by Cefoxitin for Injection and Dextrose Injection or other antibacterial drugs in the future.

Rx only

DUPLEX is a registered trademark of B. Braun Medical Inc.

Clinitest is a registered trademark of Siemens Healthcare Diagnostics Inc.

B. Braun Medical Inc.
Bethlehem, PA 18018-3524 USA
1-800-227-2862

Y36-002-978 LD-100-4

PRINCIPAL DISPLAY PANEL - 50 mL Container Label

Cefoxitin for Injection
and Dextrose Injection

1g*

REF 3123-11
NDC 0264-3123-11

DUPLEX® CONTAINER

50 mL

Use only after mixing contents of both chambers.
For IV Use Only Iso-osmotic Single-Dose Sterile/Nonpyrogenic

* Contains cefoxitin sodium equivalent to 1 g cefoxitin.

Reconstitution: Hold container with set port in a downward direction and fold
the diluent chamber just below the solution meniscus. To activate seal, squeeze
folded diluent chamber until seal between diluent and drug chamber opens,
releasing diluent into drug chamber. Agitate the reconstituted solution until the
drug powder is completely dissolved. Fold the container a second time and
squeeze until seal between drug chamber and set port opens.

After reconstitution each 50 mL single dose unit contains: Cefoxitin Sodium USP
(equivalent to 1 g cefoxitin) with approx. 2 g (4% w/v) Hydrous Dextrose USP in
Water for Injection USP. Sodium content is 53.8 mg (2.3 mEq) per gram of cefoxitin.
Approximate osmolality: 290 mOsmol/kg
Prior to Reconstitution: Store at 20-25°C (68-77°F). Excursions permitted to
15-30°C (59-86°F). [See USP Controlled Room Temperature.] Use only if container
and seals are intact. Do not peel foil strip until ready for use. After foil strip
removal, product must be used within 7 days, but not beyond the labeled
expiration date. Protect from light after removal of foil strip.
After Reconstitution: Use only if prepared solution is clear and free from
particulate matter. Use within 12 hours if stored at room temperature or within
7 days if stored under refrigeration. Do not use in a series connection. Do not
introduce additives into this container. Prior to administration check for minute
leaks by squeezing container firmly. If leaks are found, discard container and
solution as sterility may be impaired. Do not freeze.

Not made with natural rubber latex, PVC or DEHP.

Rx only

B. Braun Medical Inc.
Bethlehem, PA 18018-3524

Prepared in USA. API from USA and Italy.

Y37-002-561
LD-204-3

EXP

LOT

PEEL HERE

Drug Chamber

Discard unit if foil strip is damaged. Peel foil strip only when ready for use. Visually inspect drug prior to reconstitution.

See package insert for complete directions for reconstitution and administration.

LD-336-1 X27-001-485

PRINCIPAL DISPLAY PANEL - 50 mL Container Label-

Cefoxitin for Injection
and Dextrose Injection

2g*
REF 3125-11
NDC 0264-3125-11

DUPLEX® CONTAINER

50 mL

Use only after mixing contents of both chambers.
For IV Use Only Iso-osmotic Single-Dose Sterile/Nonpyrogenic
* Contains cefoxitin sodium equivalent to 2 g cefoxitin.

Reconstitution: Hold container with set port in a downward direction and fold
the diluent chamber just below the solution meniscus. To activate seal, squeeze
folded diluent chamber until seal between diluent and drug chamber opens,
releasing diluent into drug chamber. Agitate the reconstituted solution until the
drug powder is completely dissolved. Fold the container a second time and
squeeze until seal between drug chamber and set port opens.

After reconstitution each 50 mL single dose unit contains: Cefoxitin Sodium USP
(equivalent to 2 g cefoxitin) with approx. 1.1 g (2.2% w/v) Hydrous Dextrose USP in
Water for Injection USP. Sodium content is 53.8 mg (2.3 mEq) per gram of cefoxitin.
Approximate osmolality: 290 mOsmol/kg
Prior to Reconstitution: Store at 20-25°C (68-77°F). Excursions permitted to
15-30°C (59-86°F). [See USP Controlled Room Temperature.] Use only if container
and seals are intact. Do not peel foil strip until ready for use. After foil strip
removal, product must be used within 7 days, but not beyond the labeled
expiration date. Protect from light after removal of foil strip.
After Reconstitution: Use only if prepared solution is clear and free from
particulate matter. Use within 12 hours if stored at room temperature or within
7 days if stored under refrigeration. Do not use in a series connection. Do not
introduce additives into this container. Prior to administration check for minute
leaks by squeezing container firmly. If leaks are found, discard container and
solution as sterility may be impaired. Do not freeze.

Not made with natural rubber latex, PVC or DEHP.
Rx only

B. Braun Medical Inc.
Bethlehem, PA 18018-3524

Prepared in USA. API from USA and Italy.
Y37-002-562
LD-205-3

EXP

LOT

PEEL HERE

Drug Chamber

Discard unit if foil strip is damaged. Peel foil strip only when ready for use. Visually inspect drug prior to reconstitution.

See package insert for complete directions for reconstitution and administration.

LD-336-1 X27-001-485